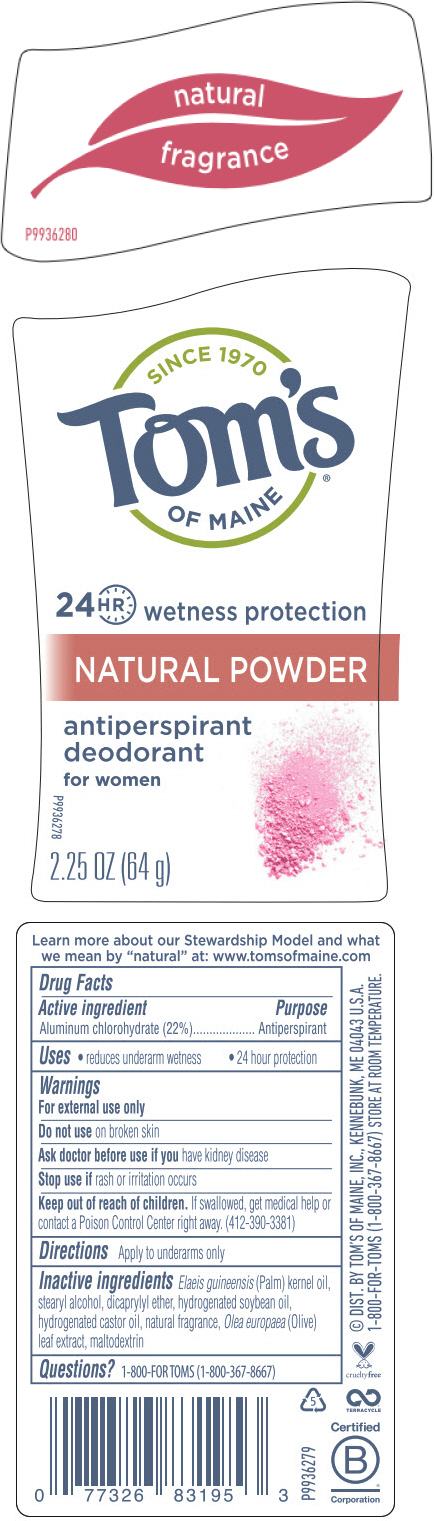 DRUG LABEL: Toms of Maine Natural Powder Antiperspirant / Deodorant
NDC: 51009-843 | Form: STICK
Manufacturer: Toms of Maine, Inc.
Category: otc | Type: HUMAN OTC DRUG LABEL
Date: 20241120

ACTIVE INGREDIENTS: ALUMINUM CHLOROHYDRATE 220 mg/1 g
INACTIVE INGREDIENTS: PALM KERNEL OIL; STEARYL ALCOHOL; DICAPRYLYL ETHER; HYDROGENATED SOYBEAN OIL; HYDROGENATED CASTOR OIL; OLEA EUROPAEA LEAF; MALTODEXTRIN

Tom's® of Maine Natural Powder Antiperspirant / Deodorant (2.25 oz)

Drug Facts

Active ingredient

Aluminum chlorohydrate (22%)

Purpose

Antiperspirant

Uses

- reduces underarm wetness
- 24 hour protection

Warnings

For external use only

Do not use on broken skin

Ask doctor before use if you have kidney disease

Stop use if rash or irritation occurs

Keep out of reach of children. If swallowed, get medical help or contact a Poison Control Center right away. (412-390-3381)

Directions

Apply to underarms only

Inactive ingredients

Elaeis guineensis (Palm) kernel oil, stearyl alcohol, dicaprylyl ether, hydrogenated soybean oil, hydrogenated castor oil, natural fragrance, Olea europaea (Olive) leaf extract, maltodextrin

Questions?

1-800-FOR TOMS (1-800-367-8667)

DIST. BY TOM'S OF MAINE, INC., KENNEBUNK, ME 04043 U.S.A.

PRINCIPAL DISPLAY PANEL - 64 g Container Label

natural
fragrance

P9936280

SINCE 1970
Tom's®
OF MAINE

24 HR wetness protection

NATURAL POWDER

antiperspirant
deodorant
for women

2.25 OZ (64 g)

P9936278